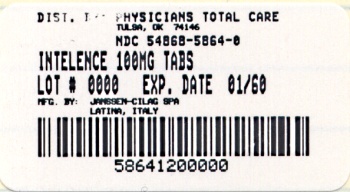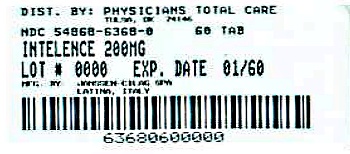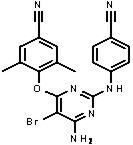 DRUG LABEL: Intelence
NDC: 54868-5864 | Form: TABLET
Manufacturer: Physicians Total Care, Inc.
Category: prescription | Type: HUMAN PRESCRIPTION DRUG LABEL
Date: 20130102

ACTIVE INGREDIENTS: etravirine 100 mg/1 1
INACTIVE INGREDIENTS: silicon dioxide; croscarmellose sodium; hypromelloses; lactose monohydrate; magnesium stearate; cellulose, microcrystalline

HIGHLIGHTS OF PRESCRIBING INFORMATION

These highlights do not include all the information needed to use INTELENCE® safely and effectively. See full prescribing information for INTELENCE®.
INTELENCE® (etravirine) tablets for oral use
Initial U.S. Approval 2008

RECENT MAJOR CHANGES

Indications and Usage (1) | 3/2012
Dosage and Administration | 3/2012
Children and Adolescents (2.2)
Method of Administration (2.3)
Warnings and Precautions
Immune Reconstitution Syndrome (5.3) | 8/2012

1 INDICATIONS AND USAGE

INTELENCE® is a human immunodeficiency virus type 1 (HIV-1) non-nucleoside reverse transcriptase inhibitor (NNRTI) indicated for treatment of HIV-1 infection in treatment-experienced patients 6 years of age and older with viral strains resistant to an NNRTI and other antiretroviral agents. (1)

In patients who have experienced virologic failure on an NNRTI-containing regimen, do not use INTELENCE® in combination with only N[t]RTIs. (1)

Treatment history and resistance testing should guide the use of INTELENCE®. (1)

2 DOSAGE AND ADMINISTRATION

- Adult patients: 200 mg (one 200 mg tablet or two 100 mg tablets) taken twice daily following a meal. (2.1, 2.3)
- Pediatric patients (6 years to less than 18 years of age and weighing at least 16 kg): dosage of INTELENCE® is based on body weight and should not exceed the recommended adult dose. (2.2, 2.3)
- INTELENCE® tablets should be taken following a meal. (2.2, 2.3)

3 DOSAGE FORMS AND STRENGTHS

25 mg tablets, 100 mg tablets and 200 mg tablets (3)

4 CONTRAINDICATIONS

None

5 WARNINGS AND PRECAUTIONS

Severe, potentially life threatening and fatal skin reactions have been reported. This includes cases of Stevens-Johnson syndrome, hypersensitivity reaction, toxic epidermal necrolysis and erythema multiforme. Immediately discontinue treatment if severe hypersensitivity, severe rash or rash with systemic symptoms or liver transaminase elevations develops and monitor clinical status, including liver transaminases closely. (5.1)

6 ADVERSE REACTIONS

The most common adverse drug reactions of moderate to severe intensity (at least 2%) which occurred at a higher rate than placebo in adults are rash and peripheral neuropathy. (6.1)

The most common adverse drug reactions in at least 2% of pediatric patients are rash and diarrhea. (6.2)

To report SUSPECTED ADVERSE REACTIONS, contact Janssen Products, LP at 1-800-JANSSEN (1-800-526-7736) or FDA at 1-800-FDA-1088 or www.fda.gov/medwatch.

7 DRUG INTERACTIONS

INTELENCE® should not be co-administered with the following antiretrovirals:

- Tipranavir/ritonavir, fosamprenavir/ritonavir, atazanavir/ritonavir
- Protease inhibitors administered without ritonavir
- NNRTIs

Co-administration of INTELENCE® with drugs that inhibit or induce CYP3A, CYP2C9, and/or CYP2C19 may alter the therapeutic effect or adverse reaction profile of etravirine. (7)

Co-administration of INTELENCE® with drugs that are substrates of CYP3A, CYP2C9, and/or CYP2C19 or are transported by P-glycoprotein may alter the therapeutic effect or adverse reaction profile of the co-administered drug(s). (7)

Refer to the Full Prescribing Information for other drugs that should not be co-administered with INTELENCE® and for other drugs that may require a change in dose or regimen. (7)

8 USE IN SPECIFIC POPULATIONS

- Nursing Mothers: Mothers should not breastfeed due to the potential for HIV transmission. (8.3)

FULL PRESCRIBING INFORMATION

1 INDICATIONS AND USAGE

INTELENCE® [Registered trademark of Tibotec Pharmaceuticals] , in combination with other antiretroviral agents, is indicated for the treatment of human immunodeficiency virus type 1 (HIV-1) infection in antiretroviral treatment-experienced patients ages 6 years and older, who have evidence of viral replication and HIV-1 strains resistant to a non-nucleoside reverse transcriptase inhibitor (NNRTI) and other antiretroviral agents.

The indication for adult use is based on Week 48 analyses from 2 randomized, double-blind, placebo-controlled trials of INTELENCE®. Both studies were conducted in clinically advanced, 3-class antiretroviral (NNRTI, N[t]RTI, PI) treatment-experienced adults. The indication for pediatric use is based on 24-week analyses of a single-arm, Phase 2 trial in antiretroviral treatment-experienced pediatric subjects 6 years to less than 18 years of age [see Use in Specific Populations (8.4)].

In treatment-experienced adult and pediatric patients, the following points should be considered when initiating therapy with INTELENCE®:

- Treatment history and resistance testing should guide the use of INTELENCE® due to concerns for potential cross-resistance [see Microbiology (12.4) and Clinical Studies (14)].
- In patients who have experienced virologic failure on an NNRTI-containing regimen, do not use INTELENCE® in combination with only N[t]RTIs [see Clinical Studies (14)].
- The use of other active antiretroviral agents with INTELENCE® is associated with an increased likelihood of treatment response.
- The safety and efficacy of INTELENCE® have not been established in pediatric patients less than 6 years of age or in treatment-naïve adult or pediatric patients.

2 DOSAGE AND ADMINISTRATION

2.1 Adult Patients

The recommended oral dose of INTELENCE® tablets is 200 mg (one 200 mg tablet or two 100 mg tablets) taken twice daily following a meal [see Clinical Pharmacology (12.3)]. The type of food does not affect the exposure to etravirine.

2.2 Pediatric Patients (6 years to less than 18 years of age)

The recommended dose of INTELENCE® for pediatric patients 6 years to less than 18 years of age and weighing at least 16 kg is based on body weight (see table below) not exceeding the recommended adult dose. INTELENCE tablet(s) should be taken orally, following a meal [see Clinical Pharmacology (12.3)]. The type of food does not affect the exposure to etravirine.

Recommended dose of INTELENCE® for pediatric patients 6 years to less than 18 years of age
Weight kilograms (kg) | Dose
greater than or equal to 16 kg to less than 20 kg | 100 mg twice daily
greater than or equal to 20 kg to less than 25 kg | 125 mg twice daily
greater than or equal to 25 kg to less than 30 kg | 150 mg twice daily
greater than or equal to 30 kg | 200 mg twice daily

The safety and efficacy of INTELENCE® have not been established in children less than 6 years of age [see Clinical Pharmacology (12.3)].

Healthcare professionals should pay special attention to the accurate dose selection of INTELENCE®, the transcription of the medication order, the dispensing information and the dosing instructions to minimize the risk of medication errors, overdosing, and underdosing.

2.3 Method of Administration

Patients should be instructed to swallow the INTELENCE® tablet(s) whole with a liquid such as water. Patients who are unable to swallow the INTELENCE® tablet(s) whole may disperse the tablet(s) in a glass of water. The patient should be instructed to do the following:

- place the tablet(s) in 5 ml (1 teaspoon) of water, or at least enough liquid to cover the medication,
- stir well until the water looks milky,
- if desired, add more water or alternatively orange juice or milk (patients should not place the tablets in orange juice or milk without first adding water). The use of grapefruit juice or warm (greater than 40°C) or carbonated beverages should be avoided.
- drink it immediately,
- rinse the glass several times with water, orange juice, or milk and completely swallow the rinse each time to make sure the patient takes the entire dose.

3 DOSAGE FORMS AND STRENGTHS

3.1 INTELENCE® 25 mg Tablets

INTELENCE® 25 mg tablets are supplied as white to off-white, oval, scored tablets debossed with "TMC" on one side.

3.2 INTELENCE® 100 mg Tablets

INTELENCE® 100 mg tablets are supplied as white to off-white oval tablets debossed with "TMC125" on one side and "100" on the other side.

3.3 INTELENCE® 200 mg Tablets

INTELENCE® 200 mg tablets are supplied as white to off-white, biconvex, oblong tablets debossed with "T200" on one side.

4 CONTRAINDICATIONS

None

5 WARNINGS AND PRECAUTIONS

5.1 Severe Skin and Hypersensitivity Reactions

Severe, potentially life-threatening, and fatal skin reactions have been reported. These include cases of Stevens-Johnson syndrome, toxic epidermal necrolysis and erythema multiforme. Hypersensitivity reactions have also been reported and were characterized by rash, constitutional findings, and sometimes organ dysfunction, including hepatic failure. In Phase 3 clinical trials, Grade 3 and 4 rashes were reported in 1.3% of subjects receiving INTELENCE® compared to 0.2% of placebo subjects. A total of 2.2% of HIV-1-infected subjects receiving INTELENCE® discontinued from Phase 3 trials due to rash [see Adverse Reactions (6)]. Rash occurred most commonly during the first 6 weeks of therapy.

Discontinue INTELENCE® immediately if signs or symptoms of severe skin reactions or hypersensitivity reactions develop (including, but not limited to, severe rash or rash accompanied by fever, general malaise, fatigue, muscle or joint aches, blisters, oral lesions, conjunctivitis, facial edema, hepatitis, eosinophilia, angioedema). Clinical status including liver transaminases should be monitored and appropriate therapy initiated. Delay in stopping INTELENCE® treatment after the onset of severe rash may result in a life-threatening reaction.

5.2 Fat Redistribution

Redistribution/accumulation of body fat, including central obesity, dorsocervical fat enlargement (buffalo hump), peripheral wasting, facial wasting, breast enlargement, and "cushingoid appearance" have been observed in patients receiving antiretroviral therapy. The mechanism and long-term consequences of these events are currently unknown. A causal relationship has not been established.

5.3 Immune Reconstitution Syndrome

Immune reconstitution syndrome has been reported in patients treated with combination antiretroviral therapy, including INTELENCE®. During the initial phase of combination antiretroviral treatment, patients whose immune system responds may develop an inflammatory response to indolent or residual opportunistic infections (such as Mycobacterium avium infection, cytomegalovirus, Pneumocystis jiroveci pneumonia (PCP) or tuberculosis), which may necessitate further evaluation and treatment.

Autoimmune disorders (such as Graves' disease, polymyositis, and Guillain-Barré syndrome) have also been reported to occur in the setting of immune reconstitution; however, the time to onset is more variable, and can occur many months after initiation of treatment.

6 ADVERSE REACTIONS

The following adverse reactions are described in greater detail in other sections:

- Severe skin and hypersensitivity reactions [see Warnings and Precautions (5.1)].

6.1 Clinical Trials Experience: Adults

Because clinical trials are conducted under widely varying conditions, adverse reaction rates observed in the clinical trials of a drug cannot be directly compared to rates in the clinical trials of another drug and may not reflect the rates observed in practice.

The safety assessment is based on all data from 1203 subjects in the Phase 3 placebo-controlled trials, TMC125-C206 and TMC125-C216, conducted in antiretroviral treatment-experienced HIV-1-infected adult subjects, 599 of whom received INTELENCE® (200 mg twice daily). In these pooled trials, the median exposure for subjects in the INTELENCE® arm and placebo arm was 52.3 and 51.0 weeks, respectively. Discontinuations due to adverse drug reactions (ADRs) were 5.2% in the INTELENCE® arm and 2.6% in the placebo arm.

The most frequently reported ADR at least Grade 2 in severity was rash (10.0%). Stevens-Johnson syndrome, drug hypersensitivity reaction and erythema multiforme were reported in less than 0.1% of subjects during clinical development with INTELENCE® [see Warnings and Precautions (5.1)]. A total of 2.2% of HIV-1-infected subjects in Phase 3 trials receiving INTELENCE® discontinued due to rash. In general, in clinical trials, rash was mild to moderate, occurred primarily in the second week of therapy, and was infrequent after Week 4. Rash generally resolved within 1 to 2 weeks on continued therapy. The incidence of rash was higher in women compared to men in the INTELENCE® arm in the Phase 3 trials. Patients with a history of NNRTI-related rash did not appear to be at increased risk for the development of INTELENCE®-related rash compared to patients without a history of NNRTI-related rash.

Common Adverse Reactions

Clinical ADRs of moderate intensity or greater (greater than or equal to Grade 2) and reported in at least 2% of subjects treated with INTELENCE® and occurring at a higher rate compared to placebo (excess of 1%) are presented in Table 1. Laboratory abnormalities considered ADRs are included in Table 2.

Table 1: Treatment-Emergent Adverse Reactions [Includes adverse reactions at least possibly, probably, or very likely related to the drug.] of at least Moderate Intensity [Intensities are defined as follows: Moderate (discomfort enough to cause interference with usual activity); Severe (incapacitating with inability to work or do usual activity).] (Grades 2 to 4) in at least 2% of Adult Subjects in the INTELENCE® Treatment Groups and at a higher rate compared to placebo (excess of 1%)
System Organ Class, Preferred Term, % | Pooled TMC125-C206 and TMC125-C216 Trials
System Organ Class, Preferred Term, % | INTELENCE® + BR N=599 | Placebo + BR N=604
Nervous System Disorders
Peripheral neuropathy | 4% | 2%
Skin and Subcutaneous Tissue Disorders
Rash | 10% | 3%
N=total number of subjects per treatment group, BR=background regimen

Less Common Adverse Reactions

Treatment-emergent ADRs occurring in less than 2% of subjects (599 subjects) receiving INTELENCE® and of at least moderate intensity (greater than or equal to Grade 2) are listed below by body system:

Cardiac Disorders: myocardial infarction, angina pectoris, atrial fibrillation

Ear and Labyrinth Disorders: vertigo

Eye Disorders: blurred vision

Gastrointestinal Disorders: gastroesophageal reflux disease, flatulence, gastritis, abdominal distension, pancreatitis, constipation, dry mouth, hematemesis, retching, stomatitis

General Disorders and Administration Site Conditions: sluggishness

Hematologic Disorders: hemolytic anemia

Hepatobiliary Disorders: hepatic failure, hepatomegaly, cytolytic hepatitis, hepatic steatosis, hepatitis

Immune System Disorders: drug hypersensitivity, immune reconstitution syndrome

Metabolism and Nutrition Disorders: diabetes mellitus, anorexia, dyslipidemia

Nervous System Disorders: paraesthesia, somnolence, convulsion, hypoesthesia, amnesia, syncope, disturbance in attention, hypersomnia, tremor

Psychiatric Disorders: anxiety, sleep disorders, abnormal dreams, confusional state, disorientation, nervousness, nightmares

Renal and Urinary Disorders: acute renal failure

Reproductive System and Breast Disorders: gynecomastia

Respiratory,Thoracic and Mediastinal Disorders: exertional dyspnea, bronchospasm

Skin and Subcutaneous Tissue Disorders: night sweats, lipohypertrophy, prurigo, hyperhidrosis, dry skin, swelling face

Additional ADRs of at least moderate intensity observed in other trials were acquired lipodystrophy, angioneurotic edema, erythema multiforme and haemorrhagic stroke, each reported in no more than 0.5% of subjects.

Laboratory Abnormalities in Treatment-Experienced Patients

Selected Grade 2 to Grade 4 laboratory abnormalities that represent a worsening from baseline observed in adult subjects treated with INTELENCE® are presented in Table 2.

Table 2: Selected Grade 2 to 4 Laboratory Abnormalities Observed in Treatment-Experienced Subjects
 |  | Pooled TMC125-C206 and TMC125-C216 Trials
Laboratory Parameter Preferred Term, % | DAIDS Toxicity Range | INTELENCE® + BR N=599 | Placebo + BR N=604
GENERAL BIOCHEMISTRY
Pancreatic amylase
Grade 2 | > 1.5–2 × ULN | 7% | 8%
Grade 3 | > 2–5 × ULN | 7% | 8%
Grade 4 | > 5 × ULN | 2% | 1%
Lipase
Grade 2 | > 1.5–3 × ULN | 4% | 6%
Grade 3 | > 3–5 × ULN | 2% | 2%
Grade 4 | > 5×ULN | 1% | < 1%
Creatinine
Grade 2 | > 1.4–1.8 × ULN | 6% | 5%
Grade 3 | > 1.9–3.4 × ULN | 2% | 1%
Grade 4 | > 3.4 × ULN | 0% | < 1%
HEMATOLOGY
Decreased hemoglobin
Grade 2 | 90–99 g/L | 2% | 4%
Grade 3 | 70–89 g/L | < 1% | < 1%
Grade 4 | < 70 g/L | < 1% | < 1%
White blood cell count
Grade 2 | 1,500–1,999/mm^3 | 2% | 3%
Grade 3 | 1,000–1,499/mm^3 | 1% | 4%
Grade 4 | < 1,000/mm^3 | 1% | < 1%
Neutrophils
Grade 2 | 750–999/mm^3 | 5% | 6%
Grade 3 | 500–749/mm^3 | 4% | 4%
Grade 4 | < 500/mm^3 | 2% | 3%
Platelet count
Grade 2 | 50,000–99,999/mm^3 | 3% | 5%
Grade 3 | 25,000–49,999/mm^3 | 1% | 1%
Grade 4 | < 25,000/mm^3 | < 1% | < 1%
LIPIDS AND GLUCOSE
Total cholesterol
Grade 2 | > 6.20–7.77 mmol/L 240–300 mg/dL | 20% | 17%
Grade 3 | > 7.77 mmol/L > 300 mg/dL | 8% | 5%
Low density lipoprotein
Grade 2 | 4.13–4.9 mmol/L 160–190 mg/dL | 13% | 12%
Grade 3 | > 4.9 mmol/L > 190 mg/dL | 7% | 7%
Triglycerides
Grade 2 | 5.65–8.48 mmol/L 500 –750 mg/dL | 9% | 7%
Grade 3 | 8.49–13.56 mmol/L 751 – 1200 mg/dL | 6% | 4%
Grade 4 | > 13.56 mmol/L > 1200 mg/dL | 4% | 2%
Elevated glucose levels
Grade 2 | 6.95–13.88 mmol/L 161–250 mg/dL | 15% | 13%
Grade 3 | 13.89–27.75 mmol/L 251 – 500 mg/dL | 4% | 2%
Grade 4 | > 27.75 mmol/L > 500 mg/dL | 0% | < 1%
HEPATIC PARAMETERS
Alanine amino transferase
Grade 2 | 2.6–5 × ULN | 6% | 5%
Grade 3 | 5.1–10 × ULN | 3% | 2%
Grade 4 | > 10 × ULN | 1% | < 1%
Aspartate amino transferase
Grade 2 | 2.6–5 × ULN | 6% | 8%
Grade 3 | 5.1–10 × ULN | 3% | 2%
Grade 4 | > 10 × ULN | < 1% | < 1%
ULN=Upper Limit of Normal, BR=background regimen

Patients co-infected with hepatitis B and/or hepatitis C virus

In Phase 3 trials TMC125-C206 and TMC125-C216, 139 subjects (12.3%) with chronic hepatitis B and/or hepatitis C virus co-infection out of 1129 subjects were permitted to enroll. AST and ALT abnormalities occurred more frequently in hepatitis B and/or hepatitis C virus co-infected subjects for both treatment groups. Grade 2 or higher laboratory abnormalities that represent a worsening from baseline of AST, ALT or total bilirubin occurred in 27.8%, 25.0% and 7.1% respectively, of INTELENCE®-treated co-infected subjects as compared to 6.7%, 7.5% and 1.8% of non-co-infected INTELENCE®-treated subjects. In general, adverse events reported by INTELENCE®-treated subjects with hepatitis B and/or hepatitis C virus co-infection were similar to INTELENCE®-treated subjects without hepatitis B and/or hepatitis C virus co-infection.

6.2 Clinical Trials Experience: Pediatric Subjects (6 years to less than 18 years of age)

The safety assessment in children and adolescents is based on the Week 24 analysis of the single-arm, Phase 2 trial TMC125-C213 in which 101 antiretroviral treatment-experienced HIV-1 infected subjects 6 years to less than 18 years of age and weighing at least 16 kg received INTELENCE in combination with other antiretroviral agents [see Clinical Studies (14.2)]. The frequency, type and severity of adverse drug reactions in pediatric subjects were comparable to those observed in adult subjects, except for rash which was observed more frequently in pediatric subjects. The most common adverse drug reactions in at least 2% of pediatric subjects were rash and diarrhea. Rash (greater than or equal to Grade 2) occurred in 15% of pediatric subjects. In the majority of cases, rash was mild to moderate, of macular/papular type, and occurred in the second week of therapy. Rash was self-limiting and generally resolved within 1 week on continued therapy. The discontinuation rate for rash was 4%. Rash including serious (Grade 3 or 4) events and discontinuations were more frequently observed in female subjects compared to male subjects.

6.3 Postmarketing Experience

The following events have been identified during postmarketing use of INTELENCE®. Because these events are reported voluntarily from a population of unknown size, it is not always possible to reliably estimate their frequency or establish a causal relationship to drug exposure.

Immune System Disorders: Severe hypersensitivity reactions including cases of hepatic failure have been reported [see Warnings and Precautions (5.1)].

Musculoskeletal and Connective Tissue Disorders: rhabdomyolysis

Skin and Subcutaneous Tissue Disorders: Fatal cases of toxic epidermal necrolysis have been reported [see Warnings and Precautions (5.1)].

7 DRUG INTERACTIONS

Etravirine is a substrate of CYP3A, CYP2C9, and CYP2C19. Therefore, co-administration of INTELENCE® with drugs that induce or inhibit CYP3A, CYP2C9, and CYP2C19 may alter the therapeutic effect or adverse reaction profile of INTELENCE® (see Table 3). [See also Clinical Pharmacology (12.3).]

Etravirine is an inducer of CYP3A and inhibitor of CYP2C9, CYP2C19 and P-glycoprotein. Therefore, co-administration of drugs that are substrates of CYP3A, CYP2C9 and CYP2C19 or are transported by P-glycoprotein with INTELENCE® may alter the therapeutic effect or adverse reaction profile of the co-administered drug(s) (see Table 3). [See also Clinical Pharmacology (12.3).]

Table 3 shows the established and other potentially significant drug interactions based on which, alterations in dose or regimen of INTELENCE® and/or co-administered drug may be recommended. Drugs that are not recommended for co-administration with INTELENCE® are also included in Table 3.

Table 3: Established and Other Potentially Significant Drug Interactions: Alterations in Dose or Regimen May Be Recommended Based on Drug Interaction Studies or Predicted Interaction [See Clinical Pharmacology (12.3)]
Concomitant Drug Class: Drug Name | Effect on Concentration of Etravirine or Concomitant Drug | Clinical Comment
HIV-Antiviral Agents: Non-Nucleoside Reverse Transcriptase Inhibitors (NNRTIs)
efavirenz [The interaction between INTELENCE® and the drug was evaluated in a clinical study. All other drug interactions shown are predicted.] nevirapine | ↓ etravirine | Combining two NNRTIs has not been shown to be beneficial. Concomitant use of INTELENCE® with efavirenz or nevirapine may cause a significant decrease in the plasma concentrations of etravirine and loss of therapeutic effect of INTELENCE®. INTELENCE® and other NNRTIs should not be co-administered.
delavirdine | ↑ etravirine | Combining two NNRTIs has not been shown to be beneficial. INTELENCE® and delavirdine should not be co-administered.
rilpivirine | ↓ rilpivirine ↔ etravirine | Combining two NNRTIs has not been shown to be beneficial. INTELENCE® and rilpivirine should not be coadministered.
HIV-Antiviral Agents: Protease Inhibitors (PIs)
atazanavir (without ritonavir) | ↓ atazanavir | Concomitant use of INTELENCE® with atazanavir without low-dose ritonavir may cause a significant alteration in the plasma concentration of atazanavir. INTELENCE® should not be co-administered with atazanavir without low-dose ritonavir.
atazanavir/ritonavir | ↓ atazanavir ↑ etravirine | Concomitant use of INTELENCE® with atazanavir/ritonavir may cause a significant decrease in atazanavir Cmin and loss of therapeutic effect of atazanavir. In addition, the mean systemic exposure (AUC) of etravirine after co-administration of INTELENCE® with atazanavir/ritonavir is anticipated to be higher than the mean systemic exposure of etravirine observed in the Phase 3 trials after co-administration of INTELENCE® and darunavir/ritonavir (as part of the background regimen). INTELENCE® and atazanavir/ritonavir should not be co-administered.
darunavir/ritonavir | ↓ etravirine | The mean systemic exposure (AUC) of etravirine was reduced when INTELENCE® was co-administered with darunavir/ritonavir. Because all subjects in the Phase 3 trials received darunavir/ritonavir as part of the background regimen and etravirine exposures from these trials were determined to be safe and effective, INTELENCE® and darunavir/ritonavir can be co-administered without dose adjustments.
fosamprenavir (without ritonavir) | ↑ amprenavir | Concomitant use of INTELENCE® with fosamprenavir without low-dose ritonavir may cause a significant alteration in the plasma concentration of amprenavir. INTELENCE® should not be co-administered with fosamprenavir without low-dose ritonavir.
fosamprenavir/ritonavir | ↑ amprenavir | Due to a significant increase in the systemic exposure of amprenavir, the appropriate doses of the combination of INTELENCE® and fosamprenavir/ritonavir have not been established. INTELENCE® and fosamprenavir/ritonavir should not be co-administered.
indinavir (without ritonavir) | ↓ indinavir | Concomitant use of INTELENCE® with indinavir without low-dose ritonavir may cause a significant alteration in the plasma concentration of indinavir. INTELENCE® should not be co-administered with indinavir without low-dose ritonavir.
lopinavir/ritonavir | ↓ etravirine | The mean systemic exposure (AUC) of etravirine was reduced after co-administration of INTELENCE® with lopinavir/ritonavir (tablet). Because the reduction in the mean systemic exposures of etravirine in the presence of lopinavir/ritonavir is similar to the reduction in mean systemic exposures of etravirine in the presence of darunavir/ritonavir, INTELENCE® and lopinavir/ritonavir can be co-administered without dose adjustments.
nelfinavir (without ritonavir) | ↑ nelfinavir | Concomitant use of INTELENCE® with nelfinavir without low-dose ritonavir may cause a significant alteration in the plasma concentration of nelfinavir. INTELENCE® should not be co-administered with nelfinavir without low-dose ritonavir.
ritonavir | ↓ etravirine | Concomitant use of INTELENCE® with ritonavir 600 mg twice daily may cause a significant decrease in the plasma concentration of etravirine and loss of therapeutic effect of INTELENCE®. INTELENCE® and ritonavir 600 mg twice daily should not be co-administered.
saquinavir/ritonavir | ↓ etravirine | The mean systemic exposure (AUC) of etravirine was reduced when INTELENCE® was co-administered with saquinavir/ritonavir. Because the reduction in the mean systemic exposures of etravirine in the presence of saquinavir/ritonavir is similar to the reduction in mean systemic exposures of etravirine in the presence of darunavir/ritonavir, INTELENCE® and saquinavir/ritonavir can be co-administered without dose adjustments.
tipranavir/ritonavir | ↓ etravirine | Concomitant use of INTELENCE® with tipranavir/ritonavir may cause a significant decrease in the plasma concentrations of etravirine and loss of therapeutic effect of INTELENCE®. INTELENCE® and tipranavir/ritonavir should not be co-administered.
CCR5 Antagonists
maraviroc | ↔ etravirine ↓ maraviroc | When INTELENCE® is co-administered with maraviroc in the absence of a potent CYP3A inhibitor (e.g., ritonavir boosted protease inhibitor), the recommended dose of maraviroc is 600 mg twice daily. No dose adjustment of INTELENCE® is needed.
maraviroc/darunavir/ritonavir | ↔ etravirine ↑ maraviroc | When INTELENCE® is co-administered with maraviroc in the presence of a potent CYP3A inhibitor (e.g., ritonavir boosted protease inhibitor), the recommended dose of maraviroc is 150 mg twice daily. No dose adjustment of INTELENCE® is needed.
Other Agents
Antiarrhythmics: digoxin | ↔ etravirine ↑ digoxin | For patients who are initiating a combination of INTELENCE® and digoxin, the lowest dose of digoxin should initially be prescribed. For patients on a stable digoxin regimen and initiating INTELENCE®, no dose adjustment of either INTELENCE® or digoxin is needed. The serum digoxin concentrations should be monitored and used for titration of the digoxin dose to obtain the desired clinical effect.
amiodarone, bepridil, disopyramide, flecainide, lidocaine (systemic), mexiletine, propafenone, quinidine | ↓ antiarrhythmics | Concentrations of these antiarrhythmics may be decreased when co-administered with INTELENCE®. INTELENCE® and antiarrhythmics should be co-administered with caution. Drug concentration monitoring is recommended, if available.
Anticoagulants: warfarin | ↑ anticoagulants | Warfarin concentrations may be increased when co-administered with INTELENCE®. The international normalized ratio (INR) should be monitored when warfarin is combined with INTELENCE®.
Anticonvulsants: carbamazepine, phenobarbital, phenytoin | ↓ etravirine | Carbamazepine, phenobarbital and phenytoin are inducers of CYP450 enzymes. INTELENCE® should not be used in combination with carbamazepine, phenobarbital, or phenytoin as co-administration may cause significant decreases in etravirine plasma concentrations and loss of therapeutic effect of INTELENCE®.
Antifungals: fluconazole, voriconazole | ↑ etravirine ↔ fluconazole ↑ voriconazole | Co-administration of etravirine and fluconazole significantly increased etravirine exposures. The amount of safety data at these increased etravirine exposures is limited, therefore, etravirine and fluconazole should be co-administered with caution. No dose adjustment of INTELENCE® or fluconazole is needed.
 |  | Co-administration of etravirine and voriconazole significantly increased etravirine exposures. The amount of safety data at these increased etravirine exposures is limited, therefore, etravirine and voriconazole should be co-administered with caution. No dose adjustment of INTELENCE® or voriconazole is needed.
Antifungals: itraconazole, ketoconazole, posaconazole | ↑ etravirine ↓ itraconazole ↓ ketoconazole ↔ posaconazole | Posaconazole, a potent inhibitor of CYP3A4, may increase plasma concentrations of etravirine. Itraconazole and ketoconazole are potent inhibitors as well as substrates of CYP3A4. Concomitant systemic use of itraconazole or ketoconazole and INTELENCE® may increase plasma concentrations of etravirine. Simultaneously, plasma concentrations of itraconazole or ketoconazole may be decreased by INTELENCE®. Dose adjustments for itraconazole, ketoconazole or posaconazole may be necessary depending on the other co-administered drugs.
Antiinfectives: clarithromycin | ↑ etravirine ↓ clarithromycin ↑ 14-OH-clarithromycin | Clarithromycin exposure was decreased by INTELENCE®; however, concentrations of the active metabolite, 14-hydroxy-clarithromycin, were increased. Because 14-hydroxy-clarithromycin has reduced activity against Mycobacterium avium complex (MAC), overall activity against this pathogen may be altered. Alternatives to clarithromycin, such as azithromycin, should be considered for the treatment of MAC.
Antimycobacterials: rifampin, rifapentine | ↓ etravirine | Rifampin and rifapentine are potent inducers of CYP450 enzymes. INTELENCE® should not be used with rifampin or rifapentine as co-administration may cause significant decreases in etravirine plasma concentrations and loss of therapeutic effect of INTELENCE®.
Antimycobacterials: rifabutin | ↓ etravirine ↓ rifabutin ↓ 25-O-desacetylrifabutin | If INTELENCE® is NOT co-administered with a protease inhibitor/ritonavir, then rifabutin at a dose of 300 mg once daily is recommended. If INTELENCE® is co-administered with darunavir/ritonavir, lopinavir/ritonavir or saquinavir/ritonavir, then rifabutin should not be co-administered due to the potential for significant reductions in etravirine exposure.
Benzodiazepines: diazepam | ↑ diazepam | Concomitant use of INTELENCE® with diazepam may increase plasma concentrations of diazepam. A decrease in diazepam dose may be needed.
Corticosteroids: dexamethasone (systemic) | ↓ etravirine | Systemic dexamethasone induces CYP3A and can decrease etravirine plasma concentrations. This may result in loss of therapeutic effect of INTELENCE®. Systemic dexamethasone should be used with caution or alternatives should be considered, particularly for long-term use.
Herbal Products: St. John's wort (Hypericum perforatum) | ↓ etravirine | Concomitant use of INTELENCE® with products containing St. John's wort may cause significant decreases in etravirine plasma concentrations and loss of therapeutic effect of INTELENCE®. INTELENCE® and products containing St. John's wort should not be co-administered.
HMG-CoA Reductase Inhibitors: atorvastatin fluvastatin, lovastatin, pitavastatin, pravastatin, rosuvastatin, simvastatin | ↔ etravirine ↓ atorvastatin ↑ 2-OH-atorvastatin ↔ etravirine ↑ fluvastatin, ↓ lovastatin, ↑ pitavastatin, ↔ pravastatin, ↔ rosuvastatin, ↓ simvastatin | The combination of INTELENCE® and atorvastatin can be given without dose adjustments, however, the dose of atorvastatin may need to be altered based on clinical response. No interaction between pravastatin, rosuvastatin and INTELENCE® is expected. Lovastatin and simvastatin are CYP3A substrates and co-administration with INTELENCE® may result in lower plasma concentrations of the HMG-CoA reductase inhibitor. Fluvastatin and pitavastatin are metabolized by CYP2C9 and co-administration with INTELENCE® may result in higher plasma concentrations of the HMG-CoA reductase inhibitor. Dose adjustments for these HMG-CoA reductase inhibitors may be necessary.
Immunosuppressants: cyclosporine, sirolimus, tacrolimus | ↓ immunosuppressant | INTELENCE® and systemic immunosuppressants should be co-administered with caution because plasma concentrations of cyclosporine, sirolimus, or tacrolimus may be affected.
Narcotic Analgesics/Treatment of Opioid Dependence: buprenorphine, buprenorphine/naloxone, methadone | ↔ etravirine ↓ buprenorphine ↔ norbuprenorphine ↔ methadone | INTELENCE® and buprenorphine (or buprenorphine/naloxone) can be co-administered without dose adjustments, however, clinical monitoring for withdrawal symptoms is recommended as buprenorphine (or buprenorphine/naloxone) maintenance therapy may need to be adjusted in some patients. INTELENCE® and methadone can be co-administered without dose adjustments, however, clinical monitoring for withdrawal symptoms is recommended as methadone maintenance therapy may need to be adjusted in some patients.
Phosphodiesterase Type 5 (PDE-5) Inhibitors: sildenafil, tadalafil, vardenafil | ↓ sildenafil ↓ N-desmethyl-sildenafil | INTELENCE® and sildenafil can be co-administered without dose adjustments, however, the dose of sildenafil may need to be altered based on clinical effect.
Platelet Aggregation Inhibitors: clopidogrel | ↓ clopidogrel (active) metabolite | Activation of clopidogrel to its active metabolite may be decreased when clopidogrel is co-administered with INTELENCE®. Alternatives to clopidogrel should be considered.
↑ = increase, ↓ = decrease, ↔ = no change

In addition to the drugs included in Table 3, the interaction between INTELENCE® and the following drugs were evaluated in clinical studies and no dose adjustment is needed for either drug [see Clinical Pharmacology (12.3)]: didanosine, enfuvirtide (ENF), ethinylestradiol/norethindrone, omeprazole, paroxetine, raltegravir, ranitidine, and tenofovir disoproxil fumarate.

8 USE IN SPECIFIC POPULATIONS

8.1 Pregnancy

TERATOGENIC EFFECTS

Pregnancy Category B

No adequate and well-controlled studies of INTELENCE® use in pregnant women have been conducted. In addition, no pharmacokinetic studies have been conducted in pregnant patients. INTELENCE® should be used during pregnancy only if the potential benefit justifies the potential risk to the fetus.

Antiretroviral Pregnancy Registry

To monitor maternal-fetal outcomes of pregnant women exposed to INTELENCE®, an Antiretroviral Pregnancy Registry has been established. Physicians are encouraged to register patients by calling 1-800-258-4263.

Animal Data

Reproductive and developmental toxicity studies were performed in rabbits (at oral doses up to 375 mg per kg per day) and rats (at oral doses up to 1000 mg per kg per day). In both species, no treatment-related embryo-fetal effects including malformations were observed. In addition, no treatment-related effects were observed in a separate pre- and postnatal study performed in rats at oral doses up to 500 mg per kg per day. The systemic drug exposures achieved in these animal studies were equivalent to those at the recommended human dose (400 mg per day).

8.3 Nursing mothers

The Centers for Disease Control and Prevention recommend that HIV-infected mothers not breastfeed their infants to avoid risking postnatal transmission of HIV. It is not known whether etravirine is secreted in human milk. Because of both the potential for HIV transmission and the potential for adverse reactions in nursing infants, mothers should be instructed not to breastfeed if they are receiving INTELENCE®.

8.4 Pediatric use

Treatment with INTELENCE® is not recommended in children less than 6 years of age. The pharmacokinetics, safety, tolerability and efficacy of INTELENCE® in children less than 6 years of age have not been established [see Clinical Pharmacology (12.3)].

The safety, pharmacokinetic profile, and virologic and immunologic responses of INTELENCE® were evaluated in treatment-experienced HIV-1-infected pediatric subjects 6 years to less than 18 years of age and weighing at least 16 kg [see Adverse Reactions (6.2), Clinical Pharmacology (12.3) and Clinical Studies (14.2)]. Frequency, type, and severity of adverse drug reactions in pediatric subjects were comparable to those observed in adults, except for rash [see Adverse Reactions (6.2)]. Please see Dosage and Administration (2.2) for dosing recommendations for pediatric subjects 6 years to less than 18 years of age and weighing at least 16 kg.

8.5 Geriatric use

Clinical studies of INTELENCE® did not include sufficient numbers of subjects aged 65 and over to determine whether they respond differently from younger subjects. Other reported clinical experience has not identified differences in responses between the elderly and younger subjects. In general, dose selection for an elderly patient should be cautious, reflecting the greater frequency of decreased hepatic, renal, or cardiac function, and of concomitant disease or other drug therapy.

8.6 Hepatic Impairment

No dose adjustment of INTELENCE® is required in patients with mild (Child-Pugh Class A) or moderate (Child-Pugh Class B) hepatic impairment. The pharmacokinetics of INTELENCE® have not been evaluated in patients with severe hepatic impairment (Child-Pugh Class C).

8.7 Renal Impairment

Since the renal clearance of etravirine is negligible (less than 1.2%), a decrease in total body clearance is not expected in patients with renal impairment. No dose adjustments are required in patients with renal impairment. As etravirine is highly bound to plasma proteins, it is unlikely that it will be significantly removed by hemodialysis or peritoneal dialysis.

10 OVERDOSAGE

There is no specific antidote for overdose with INTELENCE®. Human experience of overdose with INTELENCE® is limited. The highest dose studied in healthy volunteers was 400 mg once daily. Treatment of overdose with INTELENCE® consists of general supportive measures including monitoring of vital signs and observation of the clinical status of the patient. If indicated, elimination of unabsorbed active substance is to be achieved by emesis or gastric lavage. Administration of activated charcoal may also be used to aid in removal of unabsorbed active substance. Because etravirine is highly protein bound, dialysis is unlikely to result in significant removal of the active substance.

11 DESCRIPTION

INTELENCE® (etravirine) is a non-nucleoside reverse transcriptase inhibitor (NNRTI) of human immunodeficiency virus type 1 (HIV-1).

The chemical name for etravirine is 4-[[6-amino-5-bromo-2-[(4-cyanophenyl)amino]-4-pyrimidinyl]oxy]-3,5-dimethylbenzonitrile. Its molecular formula is C20H15BrN6O and its molecular weight is 435.28. Etravirine has the following structural formula:

Etravirine is a white to slightly yellowish brown powder. Etravirine is practically insoluble in water over a wide pH range. It is very slightly soluble in propylene glycol and slightly soluble in ethanol. Etravirine is soluble in polyethylene glycol (PEG)400 and freely soluble in some organic solvents (e.g., N,N-dimethylformamide and tetrahydrofuran).

INTELENCE® 25 mg tablets are available as white to off-white, oval scored tablets for oral administration. Each 25 mg tablet contains 25 mg of etravirine and the inactive ingredients hypromellose, microcrystalline cellulose, colloidal silicon dioxide, croscarmellose sodium, magnesium stearate and lactose monohydrate.

INTELENCE® 100 mg tablets are available as white to off-white, oval tablets for oral administration. Each 100 mg tablet contains 100 mg of etravirine and the inactive ingredients hypromellose, microcrystalline cellulose, colloidal silicon dioxide, croscarmellose sodium, magnesium stearate and lactose monohydrate.

INTELENCE® 200 mg tablets are available as white to off-white, biconvex, oblong tablets for oral administration. Each 200 mg tablet contains 200 mg of etravirine and the inactive ingredients hypromellose, silicified microcrystalline cellulose, microcrystalline cellulose, colloidal silicon dioxide, croscarmellose sodium and magnesium stearate.

12 CLINICAL PHARMACOLOGY

12.1 Mechanism of Action

Etravirine is an antiviral drug [see Microbiology (12.4)].

12.2 Pharmacodynamics

Effects on Electrocardiogram

In a randomized, double-blind, active, and placebo-controlled crossover study, 41 healthy subjects were administered INTELENCE® 200 mg twice daily, INTELENCE® 400 mg once daily, placebo, and moxifloxacin 400 mg. After 8 days of dosing, etravirine did not prolong the QT interval. The maximum mean (upper 1-sided 95% CI) baseline and placebo-adjusted QTcF were 0.6 ms (3.3 ms) for 200 mg twice daily and -1.0 ms (2.5 ms) for 400 mg once daily dosing regimens.

12.3 Pharmacokinetics

Pharmacokinetics in Adults

The pharmacokinetic properties of INTELENCE® were determined in healthy adult subjects and in treatment-experienced HIV-1-infected adult and pediatric subjects. The systemic exposures (AUC) to etravirine were lower in HIV-1-infected subjects than in healthy subjects.

Table 4: Population Pharmacokinetic Estimates of Etravirine 200 mg twice daily in HIV-1-Infected Adult Subjects (Integrated Data from Phase 3 Trials at Week 48) [All HIV-1-infected subjects enrolled in Phase 3 clinical trials received darunavir/ritonavir 600/100 mg twice daily as part of their background regimen. Therefore, the pharmacokinetic parameter estimates shown in Table 4 account for reductions in the pharmacokinetic parameters of etravirine due to co-administration of INTELENCE® with darunavir/ritonavir.]
Parameter | Etravirine 200 mg twice daily N = 575
AUC12h (ng∙h/mL)
Geometric Mean ± Standard Deviation | 4522 ± 4710
Median (Range) | 4380 (458 – 59084)
C0h (ng/mL)
Geometric Mean ± Standard Deviation | 297 ± 391
Median (Range) | 298 (2 – 4852)

Note: The median protein binding adjusted EC50 for MT4 cells infected with HIV-1/IIIB in vitro equals 4 ng per mL.

Absorption and Bioavailability

Following oral administration, etravirine was absorbed with a Tmax of about 2.5 to 4 hours. The absolute oral bioavailability of INTELENCE® is unknown.

In healthy subjects, the absorption of etravirine is not affected by co-administration of oral ranitidine or omeprazole, drugs that increase gastric pH.

Effects of Food on Oral Absorption

The systemic exposure (AUC) to etravirine was decreased by about 50% when INTELENCE® was administered under fasting conditions, as compared to when INTELENCE® was administered following a meal. Therefore, INTELENCE® should always be taken following a meal. Within the range of meals studied, the systemic exposures to etravirine were similar. The total caloric content of the various meals evaluated ranged from 345 kilocalories (17 grams fat) to 1160 kilocalories (70 grams fat) [see Dosage and Administration (2)].

Distribution

Etravirine is about 99.9% bound to plasma proteins, primarily to albumin (99.6%) and alpha 1-acid glycoprotein (97.66% to 99.02%) in vitro. The distribution of etravirine into compartments other than plasma (e.g., cerebrospinal fluid, genital tract secretions) has not been evaluated in humans.

Metabolism

In vitro experiments with human liver microsomes (HLMs) indicate that etravirine primarily undergoes metabolism by CYP3A, CYP2C9, and CYP2C19 enzymes. The major metabolites, formed by methyl hydroxylation of the dimethylbenzonitrile moiety, were at least 90% less active than etravirine against wild-type HIV in cell culture.

Elimination

After single dose oral administration of 800 mg ^14C-etravirine, 93.7% and 1.2% of the administered dose of ^1^4C-etravirine was recovered in the feces and urine, respectively. Unchanged etravirine accounted for 81.2% to 86.4% of the administered dose in feces. Unchanged etravirine was not detected in urine. The mean (± standard deviation) terminal elimination half-life of etravirine was about 41 (± 20) hours.

Special Populations

Hepatic Impairment

Etravirine is primarily metabolized by the liver. The steady state pharmacokinetic parameters of etravirine were similar after multiple dose administration of INTELENCE® to subjects with normal hepatic function (16 subjects), mild hepatic impairment (Child-Pugh Class A, 8 subjects), and moderate hepatic impairment (Child-Pugh Class B, 8 subjects). The effect of severe hepatic impairment on the pharmacokinetics of etravirine has not been evaluated.

Hepatitis B and/or Hepatitis C Virus Co-infection

Population pharmacokinetic analysis of the TMC125-C206 and TMC125-C216 trials showed reduced clearance for etravirine in HIV-1-infected subjects with hepatitis B and/or C virus co-infection. Based upon the safety profile of INTELENCE® [see Adverse Reactions (6)], no dose adjustment is necessary in patients co-infected with hepatitis B and/or C virus.

Renal Impairment

The pharmacokinetics of etravirine have not been studied in patients with renal impairment. The results from a mass balance study with ^14C-etravirine showed that less than 1.2% of the administered dose of etravirine is excreted in the urine as metabolites. No unchanged drug was detected in the urine. As etravirine is highly bound to plasma proteins, it is unlikely that it will be significantly removed by hemodialysis or peritoneal dialysis.

Gender

No significant pharmacokinetic differences have been observed between males and females.

Race

Population pharmacokinetic analysis of etravirine in HIV-infected subjects did not show an effect of race on exposure to etravirine.

Geriatric Patients

Population pharmacokinetic analysis in HIV-infected subjects showed that etravirine pharmacokinetics are not considerably different within the age range (18 to 77 years) evaluated [see Use in Specific Populations (8.5)].

Pediatric Patients

The pharmacokinetics of etravirine in 101 treatment-experienced HIV-1-infected pediatric subjects, 6 years to less than 18 years of age and weighing at least 16 kg showed that the administered weight-based dosages (approximately 5.2 mg per kg twice daily up to the adult recommended doses) resulted in etravirine exposure comparable to that in adults receiving INTELENCE® 200 mg twice daily [see Dosage and Administration (2.2)] when administered at a dose corresponding to 5.2 mg per kg twice daily. The population pharmacokinetic estimates for etravirine AUC12h and C0h are summarized in the table below.

Population pharmacokinetic estimates for etravirine (all doses combined) in treatment-experienced HIV-1-infected pediatric subjects 6 years to less than 18 years of age (TMC125-C213)
Parameter | N = 101
AUC12h (ng•h/ml)
Geometric Mean ± Standard Deviation | 3742 ± 4314
Median (Range) | 4499 (62 – 28865)
C0h (ng•h/ml)
Geometric Mean ± Standard Deviation | 205 ± 342
Median (Range) | 287 (2 – 2276)

The pharmacokinetics of etravirine in pediatric subjects less than 6 years of age have not been established.

Drug Interactions

[See also Drug Interactions (7).]

Etravirine is a substrate of CYP3A, CYP2C9, and CYP2C19. Therefore, co-administration of INTELENCE® with drugs that induce or inhibit CYP3A, CYP2C9, and CYP2C19 may alter the therapeutic effect or adverse reaction profile of INTELENCE®.

Etravirine is an inducer of CYP3A and inhibitor of CYP2C9, CYP2C19 and P-glycoprotein. Therefore, co-administration of drugs that are substrates of CYP3A, CYP2C9 and CYP2C19 or are transported by P-glycoprotein with INTELENCE® may alter the therapeutic effect or adverse reaction profile of the co-administered drug(s).

Drug interaction studies were performed with INTELENCE® and other drugs likely to be co-administered and some drugs commonly used as probes for pharmacokinetic interactions. The effects of co-administration of other drugs on the AUC, Cmax, and Cmin values of etravirine are summarized in Table 5 (effect of other drugs on INTELENCE®). The effect of co-administration of INTELENCE® on the AUC, Cmax, and Cmin values of other drugs are summarized in Table 6 (effect of INTELENCE® on other drugs). For information regarding clinical recommendations, see Drug Interactions (7).

Table 5: Drug Interactions: Pharmacokinetic Parameters for Etravirine in the Presence of Co-administered Drugs
Co-administered Drug | Dose/Schedule of Co-administered Drug | N | Exposure | Mean Ratio of Etravirine Pharmacokinetic Parameters 90% CI; No Effect = 1.00
Co-administered Drug | Dose/Schedule of Co-administered Drug | N | Exposure | Cmax | AUC | Cmin
Co-Administration With Protease Inhibitors (PIs)
Atazanavir | 400 mg q.d. | 14 | ↑ | 1.47 (1.36–1.59) | 1.50 (1.41–1.59) | 1.58 (1.46–1.70)
Atazanavir/ ritonavir | 300/100 mg q.d. | 14 | ↑ | 1.30 (1.17–1.44) | 1.30 (1.18–1.44) | 1.26 (1.12–1.42)
Darunavir/ ritonavir | 600/100 mg b.i.d. | 14 | ↓ | 0.68 (0.57–0.82) | 0.63 (0.54–0.73) | 0.51 (0.44–0.61)
Lopinavir/ ritonavir (tablet) | 400/100 mg b.i.d. | 16 | ↓ | 0.70 (0.64–0.78) | 0.65 (0.59–0.71) | 0.55 (0.49–0.62)
Ritonavir | 600 mg b.i.d. | 11 | ↓ | 0.68 (0.55–0.85) | 0.54 (0.41–0.73) | N.A.
Saquinavir/ ritonavir | 1000/100 mg b.i.d. | 14 | ↓ | 0.63 (0.53–0.75) | 0.67 (0.56–0.80) | 0.71 (0.58–0.87)
Tipranavir/ ritonavir | 500/200 mg b.i.d. | 19 | ↓ | 0.29 (0.22–0.40) | 0.24 (0.18–0.33) | 0.18 (0.13–0.25)
Co-Administration With Nucleoside Reverse Transcriptase Inhibitors (NRTIs)
Didanosine | 400 mg q.d. | 15 | ↔ | 1.16 (1.02–1.32) | 1.11 (0.99–1.25) | 1.05 (0.93–1.18)
Tenofovir disoproxil fumarate | 300 mg q.d. | 23 | ↓ | 0.81 (0.75–0.88) | 0.81 (0.75–0.88) | 0.82 (0.73–0.91)
Co-Administration With CCR5 Antagonists
Maraviroc | 300 mg b.i.d. | 14 | ↔ | 1.05 (0.95–1.17) | 1.06 (0.99–1.14) | 1.08 (0.98–1.19)
Maraviroc (when co-administered with darunavir/ritonavir) [The reference for etravirine exposure is the pharmacokinetic parameters of etravirine in the presence of darunavir/ritonavir.] | 150/600/100 mg b.i.d. | 10 | ↔ | 1.08 (0.98–1.20) | 1.00 (0.86–1.15) | 0.81 (0.65–1.01)
Co-Administration With Integrase Strand Transfer Inhibitors
Raltegravir | 400 mg b.i.d. | 19 | ↔ | 1.04 (0.97–1.12) | 1.10 (1.03–1.16) | 1.17 (1.10–1.26)
Co-Administration With Other Drugs
Atorvastatin | 40 mg q.d. | 16 | ↔ | 0.97 (0.93–1.02) | 1.02 (0.97–1.07) | 1.10 (1.02–1.19)
Clarithromycin | 500 mg b.i.d. | 15 | ↑ | 1.46 (1.38–1.56) | 1.42 (1.34–1.50) | 1.46 (1.36–1.58)
Fluconazole | 200 mg q.a.m. | 16 | ↑ | 1.75 (1.60–1.91) | 1.86 (1.73–2.00) | 2.09 (1.90–2.31)
Omeprazole | 40 mg q.d. | 18 | ↑ | 1.17 (0.96–1.43) | 1.41 (1.22–1.62) | N.A.
Paroxetine | 20 mg q.d. | 16 | ↔ | 1.05 (0.96–1.15) | 1.01 (0.93–1.10) | 1.07 (0.98–1.17)
Ranitidine | 150 mg b.i.d. | 18 | ↓ | 0.94 (0.75–1.17) | 0.86 (0.76–0.97) | N.A.
Rifabutin | 300 mg q.d. | 12 | ↓ | 0.63 (0.53–0.74) | 0.63 (0.54–0.74) | 0.65 (0.56–0.74)
Voriconazole | 200 mg b.i.d. | 16 | ↑ | 1.26 (1.16–1.38) | 1.36 (1.25–1.47) | 1.52 (1.41–1.64)
CI = Confidence Interval; N = number of subjects with data; N.A. = not available; ↑ = increase; ↓ = decrease; ↔ = no change; q.d. = once daily; b.i.d. = twice daily; q.a.m. = once daily in the morning

Table 6: Drug Interactions: Pharmacokinetic Parameters for Co-administered Drugs in the Presence of INTELENCE®
Co-administered Drug | Dose/Schedule of Co-administered Drug | N | Exposure | Mean Ratio of Co-administered Drug Pharmacokinetic Parameters 90% CI; No effect = 1.00
Co-administered Drug | Dose/Schedule of Co-administered Drug | N | Exposure | Cmax | AUC | Cmin
Co-Administration With Protease Inhibitors (PIs)
Atazanavir | 400 mg q.d. | 14 | ↓ | 0.97 (0.73–1.29) | 0.83 (0.63–1.09) | 0.53 (0.38–0.73)
Atazanavir/ ritonavir | 300/100 mg q.d. | 13 | ↓ | 0.97 (0.89–1.05) | 0.86 (0.79–0.93) | 0.62 (0.55–0.71)
Darunavir/ ritonavir | 600/100 mg b.i.d. | 15 | ↔ | 1.11 (1.01–1.22) | 1.15 (1.05–1.26) | 1.02 (0.90–1.17)
Fosamprenavir/ ritonavir | 700/100 mg b.i.d. | 8 | ↑ | 1.62 (1.47–1.79) | 1.69 (1.53–1.86) | 1.77 (1.39–2.25)
Lopinavir/ ritonavir (tablet) | 400/100 mg b.i.d. | 16 | ↔ | 0.89 (0.82–0.96) | 0.87 (0.83–0.92) | 0.80 (0.73–0.88)
Saquinavir/ ritonavir | 1000/100 mg b.i.d. | 15 | ↔ | 1.00 (0.70–1.42) | 0.95 (0.64–1.42) | 0.80 (0.46–1.38)
Tipranavir/ ritonavir | 500/200 mg b.i.d. | 19 | ↑ | 1.14 (1.02–1.27) | 1.18 (1.03–1.36) | 1.24 (0.96–1.59)
Co-Administration With Nucleoside Reverse Transcriptase Inhibitors (NRTIs)
Didanosine | 400 mg q.d. | 14 | ↔ | 0.91 (0.58–1.42) | 0.99 (0.79–1.25) | N.A.
Tenofovir disoproxil fumarate | 300 mg q.d. | 19 | ↔ | 1.15 (1.04–1.27) | 1.15 (1.09–1.21) | 1.19 (1.13–1.26)
Co-Administration With CCR5 Antagonists
Maraviroc | 300 mg b.i.d. | 14 | ↓ | 0.40 (0.28–0.57) | 0.47 (0.38–0.58) | 0.61 (0.53–0.71)
Maraviroc (when co-administered with darunavir/ritonavir) [compared to maraviroc 150 mg b.i.d.] | 150/600/100 mg b.i.d. | 10 | ↑ | 1.77 (1.20–2.60) | 3.10 (2.57–3.74) | 5.27 (4.51–6.15)
Co-Administration With Integrase Strand Transfer Inhibitors
Raltegravir | 400 mg b.i.d. | 19 | ↓ | 0.89 (0.68–1.15) | 0.90 (0.68–1.18) | 0.66 (0.34–1.26)
Co-Administration With Other Drugs
Atorvastatin | 40 mg q.d. | 16 | ↓ | 1.04 (0.84–1.30) | 0.63 (0.58–0.68) | N.A.
2-hydroxy-atorvastatin |  | 16 | ↑ | 1.76 (1.60–1.94) | 1.27 (1.19–1.36) | N.A.
Buprenorphine | Individual dose regimen ranging from 4/1 mg to 16/4 mg q.d. | 16 | ↓ | 0.89 (0.76–1.05) | 0.75 (0.66–0.84) | 0.60 (0.52–0.68)
Norbuprenorphine |  | 16 | ↔ | 1.08 (0.95–1.23) | 0.88 (0.81–0.96) | 0.76 (0.67–0.87)
Clarithromycin | 500 mg b.i.d. | 15 | ↓ | 0.66 (0.57–0.77) | 0.61 (0.53–0.69) | 0.47 (0.38–0.57)
14-hydroxy-clarithromycin |  | 15 | ↑ | 1.33 (1.13–1.56) | 1.21 (1.05–1.39) | 1.05 (0.90–1.22)
Digoxin | 0.5 mg single dose | 16 | ↑ | 1.19 (0.96–1.49) | 1.18 (0.90–1.56) | N.A.
Ethinylestradiol | 0.035 mg q.d. | 16 | ↑ | 1.33 (1.21–1.46) | 1.22 (1.13–1.31) | 1.09 (1.01–1.18)
Norethindrone | 1 mg q.d. | 16 | ↔ | 1.05 (0.98–1.12) | 0.95 (0.90–0.99) | 0.78 (0.68–0.90)
Fluconazole | 200 mg q.a.m. | 15 | ↔ | 0.92 (0.85–1.00) | 0.94 (0.88–1.01) | 0.91 (0.84–0.98)
R(-) Methadone | Individual dose regimen ranging from 60 to 130 mg/day | 16 | ↔ | 1.02 (0.96–1.09) | 1.06 (0.99–1.13) | 1.10 (1.02–1.19)
S(+) Methadone |  | 16 | ↔ | 0.89 (0.83–0.97) | 0.89 (0.82–0.96) | 0.89 (0.81–0.98)
Paroxetine | 20 mg q.d. | 16 | ↔ | 1.06 (0.95–1.20) | 1.03 (0.90–1.18) | 0.87 (0.75–1.02)
Rifabutin | 300 mg q.d. | 12 | ↓ | 0.90 (0.78–1.03) | 0.83 (0.75–0.94) | 0.76 (0.66–0.87)
25-O-desacetylrifabutin | 300 mg q.d. | 12 | ↓ | 0.85 (0.72–1.00) | 0.83 (0.74–0.92) | 0.78 (0.70–0.87)
Sildenafil | 50 mg single dose | 15 | ↓ | 0.55 (0.40–0.75) | 0.43 (0.36–0.51) | N.A.
N-desmethyl-sildenafil |  | 15 | ↓ | 0.75 (0.59–0.96) | 0.59 (0.52–0.68) | N.A.
Voriconazole | 200 mg b.i.d. | 14 | ↑ | 0.95 (0.75–1.21) | 1.14 (0.88–1.47) | 1.23 (0.87–1.75)
CI = Confidence Interval; N = number of subjects with data; N.A. = not available; ↑ = increase; ↓ = decrease; ↔ = no change; q.d. = once daily ; b.i.d. = twice daily; q.a.m. = once daily in the morning

12.4 Microbiology

Mechanism of Action

Etravirine is an NNRTI of human immunodeficiency virus type 1 (HIV-1). Etravirine binds directly to reverse transcriptase (RT) and blocks the RNA-dependent and DNA-dependent DNA polymerase activities by causing a disruption of the enzyme's catalytic site. Etravirine does not inhibit the human DNA polymerases α, β, and γ.

Antiviral Activity in Cell Culture

Etravirine exhibited activity against laboratory strains and clinical isolates of wild-type HIV-1 in acutely infected T-cell lines, human peripheral blood mononuclear cells, and human monocytes/macrophages with median EC50 values ranging from 0.9 to 5.5 nM (i.e., 0.4 to 2.4 ng per mL). Etravirine demonstrated antiviral activity in cell culture against a broad panel of HIV-1 group M isolates (subtype A, B, C, D, E, F, G) with EC50 values ranging from 0.29 to 1.65 nM and EC50 values ranging from 11.5 to 21.7 nM against group O primary isolates. Etravirine did not show antagonism when studied in combination with the following antiretroviral drugs—the NNRTIs delavirdine, efavirenz, and nevirapine; the N(t)RTIs abacavir, didanosine, emtricitabine, lamivudine, stavudine, tenofovir, zalcitabine, and zidovudine; the PIs amprenavir, atazanavir, darunavir, indinavir, lopinavir, nelfinavir, ritonavir, saquinavir, and tipranavir; the fusion inhibitor enfuvirtide; the integrase strand transfer inhibitor raltegravir and the CCR5 co-receptor antagonist maraviroc.

Resistance

In Cell Culture

Etravirine-resistant strains were selected in cell culture originating from wild-type HIV-1 of different origins and subtypes, as well as NNRTI resistant HIV-1. Development of reduced susceptibility to etravirine typically required more than one substitution in reverse transcriptase of which the following were observed most frequently: L100I, E138K, E138G, V179I, Y181C, and M230I.

In Treatment-Experienced Subjects

In the Phase 3 trials TMC125-C206 and TMC125-C216, substitutions that developed most commonly in subjects with virologic failure at Week 48 to the INTELENCE®-containing regimen were V179F, V179I, and Y181C which usually emerged in a background of multiple other NNRTI resistance-associated substitutions. In all the trials conducted with INTELENCE® in HIV-1 infected subjects, the following substitutions emerged most commonly: L100I, E138G, V179F, V179I, Y181C and H221Y. Other NNRTI-resistance associated substitutions which emerged on etravirine treatment in less than 10% of the virologic failure isolates included K101E/H/P, K103N/R, V106I/M, V108I, Y181I, Y188L, V189I, G190S/C, N348I and R356K. The emergence of NNRTI substitutions on etravirine treatment contributed to decreased susceptibility to etravirine with a median fold-change in etravirine susceptibility of 40-fold from reference and a median fold-change of 6-fold from baseline.

Cross-Resistance

Site-Directed NNRTI Mutant Virus

Etravirine showed antiviral activity against 55 of 65 HIV-1 strains (85%) with single amino acid substitutions at RT positions associated with NNRTI resistance, including the most commonly found K103N. The single amino acid substitutions associated with an etravirine reduction in susceptibility greater than 3-fold were K101A, K101P, K101Q, E138G, E138Q, Y181C, Y181I, Y181T, Y181V, and M230L, and of these, the greatest reductions were Y181I (13-fold change in EC50 value) and Y181V (17-fold change in EC50 value). Mutant strains containing a single NNRTI resistance associated substitution (K101P, K101Q, E138Q, or M230L) had cross-resistance between etravirine and efavirenz. The majority (39 of 61; 64%) of the NNRTI mutant viruses with 2 or 3 amino acid substitutions associated with NNRTI resistance had decreased susceptibility to etravirine (fold-change greater than 3). The highest levels of resistance to etravirine were observed for HIV-1 harboring a combination of substitutions V179F + Y181C (187 fold-change), V179F + Y181I (123 fold-change), or V179F + Y181C + F227C (888 fold-change).

Clinical Isolates

Etravirine retained a fold-change less than or equal to 3 against 60% of 6171 NNRTI-resistant clinical isolates. In the same panel, the proportion of clinical isolates resistant to delavirdine, efavirenz and/or nevirapine (defined as a fold-change above their respective biological cutoff values in the assay) was 79%, 87%, and 95%, respectively. In TMC125-C206 and TMC125-C216, 34% of the baseline isolates had decreased susceptibility to etravirine (fold-change greater than 3) and 60%, 69%, and 78% of all baseline isolates were resistant to delavirdine, efavirenz, and nevirapine, respectively. Of subjects who received etravirine and were virologic failures in TMC125-C206 and TMC125-C216, 90%, 84%, and 96% of viral isolates obtained at the time of treatment failure were resistant to delavirdine, efavirenz, and nevirapine, respectively. Therefore, cross-resistance to delavirdine, efavirenz, and/or nevirapine is expected after virologic failure with an etravirine-containing regimen for the virologic failure isolates.

Treatment-naïve HIV-1-infected subjects in the Phase 3 trials for EDURANT (rilpivirine)

There are currently no clinical data available on the use of etravirine in subjects who experienced virologic failure on a rilpivirine-containing regimen. However, in the rilpivirine adult clinical development program, there was evidence of phenotypic cross-resistance between rilpivirine and etravirine. In the pooled analyses of the Phase 3 clinical trials for rilpivirine, 38 rilpivirine virologic failure subjects had evidence of HIV-1 strains with genotypic and phenotypic resistance to rilpivirine. Of these subjects, 89% (34 subjects) of virologic failure isolates were cross-resistant to etravirine based on phenotype data. Consequently, it can be inferred that cross-resistance to etravirine is likely after virologic failure and development of rilpivirine resistance. Refer to the prescribing information for EDURANT (rilpivirine) for further information.

Baseline Genotype/Phenotype and Virologic Outcome Analyses

In TMC125-C206 and TMC125-C216, the presence at baseline of the substitutions L100I, E138A, I167V, V179D, V179F, Y181I, Y181V, or G190S was associated with a decreased virologic response to etravirine. Additional substitutions associated with a decreased virologic response to etravirine when in the presence of 3 or more additional 2008 IAS-USA defined NNRTI substitutions include A98G, K101H, K103R, V106I, V179T, and Y181C. The presence of K103N, which was the most prevalent NNRTI substitution in TMC125-C206 and TMC125-C216 at baseline, did not affect the response in the INTELENCE® arm. Overall, response rates to etravirine decreased as the number of baseline NNRTI substitutions increased (shown as the proportion of subjects achieving viral load less than 50 plasma HIV RNA copies per mL at Week 48) (Table 7).

Table 7: Proportion of Subjects with less than 50 HIV-1 RNA copies per mL at Week 48 by Baseline Number of IAS-USA-Defined NNRTI Substitutions in the Non-VF Excluded Population of the Pooled TMC125-C206 and TMC125-C216 Trials
# IAS-USA-Defined NNRTI substitutions [2008 IAS-USA defined substitutions = V90I, A98G, L100I, K101E/H/P, K103N, V106A/I/M, V108I, E138A, V179D/F/T, Y181C/I/V, Y188C/H/L, G190A/S, P225H, M230L] | Etravirine Arms N = 561
 | Re-Used/Not Used Enfuvirtide | De Novo Enfuvirtide
All ranges | 61% (254/418) | 76% (109/143)
0 | 68% (52/76) | 95% (20/21)
1 | 67% (72/107) | 77% (24/31)
2 | 64% (75/118) | 86% (38/44)
3 | 55% (36/65) | 62% (16/26)
≥ 4 | 37% (19/52) | 52% (11/21)
 | Placebo Arms N = 592
All ranges | 34% (147/435) | 59% (93/157)

Response rates assessed by baseline etravirine phenotype are shown in Table 8. These baseline phenotype groups are based on the select subject populations in TMC125-C206 and TMC125-C216 and are not meant to represent definitive clinical susceptibility breakpoints for INTELENCE®. The data are provided to give clinicians information on the likelihood of virologic success based on pre-treatment susceptibility to etravirine in treatment-experienced patients.

Table 8: Proportion of Subjects with less than 50 HIV-1 RNA copies per mL at Week 48 by Baseline Phenotype and Enfuvirtide Use in the Pooled TMC125-C206 and TMC125-C216 Trials [Non-VF excluded analysis]
Etravirine Fold Change | Etravirine Arms N = 559
 | Re-Used/Not Used Enfuvirtide | De Novo Enfuvirtide | Clinical Response Range
All ranges | 61% (253/416) | 76% (109/143) | Overall Response
0 – 3 | 69% (188/274) | 83% (75/90) | Higher than Overall Response
> 3 – 13 | 50% (39/78) | 66% (25/38) | Lower than Overall Response
> 13 | 41% (26/64) | 60% (9/15) | Lower than Overall Response
 | Placebo Arms N = 583
All ranges | 34% (145/429) | 60% (92/154)

The proportion of virologic responders (viral load less than 50 HIV-1 RNA copies per mL) by the phenotypic susceptibility score (PSS) of the background therapy, including enfuvirtide, is shown in Table 9.

Table 9: Virologic Response (Viral Load less than 50 HIV-1 RNA copies per mL) at Week 48 by Phenotypic Susceptibility Score in the Non-VF Excluded Population of TMC125-C206 and TMC125-C216 Trials (Pooled Analysis)
 | INTELENCE® + BR N=559 | Placebo + BR N=586
PSS [The phenotypic susceptibility score (PSS) was defined as the total number of active antiretroviral drugs in the background therapy to which a subject's baseline viral isolate showed sensitivity in phenotypic resistance tests. Each drug in the background therapy was scored as a '1' or '0' based on whether the viral isolate was considered susceptible or resistant to that drug, respectively. In the calculation of the PSS, darunavir was counted as a sensitive antiretroviral if the FC was less than or equal to 10; enfuvirtide was counted as a sensitive antiretroviral if it had not been used previously. INTELENCE® was not included in this calculation.]
0 | 43% (40/93) | 5% (5/95)
1 | 61% (125/206) | 28% (64/226)
2 | 77% (114/149) | 59% (97/165)
≥ 3 | 75% (83/111) | 72% (72/100)

13 NONCLINICAL TOXICOLOGY

13.1 Carcinogenesis, Mutagenesis, Impairment of Fertility

Carcinogenesis

Etravirine was evaluated for carcinogenic potential by oral gavage administration to mice and rats for up to approximately 104 weeks. Daily doses of 50, 200 and 400 mg per kg were administered to mice and doses of 70, 200 and 600 mg per kg were administered to rats in the initial period of approximately 41 to 52 weeks. The high and middle doses were subsequently adjusted due to tolerability and reduced by 50% in mice and by 50 to 66% in rats to allow for completion of the studies. In the mouse study, statistically significant increases in the incidences of hepatocellular carcinoma and incidences of hepatocellular adenomas or carcinomas combined were observed in treated females. In the rat study, no statistically significant increases in tumor findings were observed in either sex. The relevance of these liver tumor findings in mice to humans is not known. Because of tolerability of the formulation in these rodent studies, maximum systemic drug exposures achieved at the doses tested were lower than those in humans at the clinical dose (400 mg per day), with animal vs. human AUC ratios being 0.6-fold (mice) and 0.2–0.7-fold (rats).

Mutagenesis

Etravirine tested negative in the in vitro Ames reverse mutation assay, in vitro chromosomal aberration assay in human lymphocyte, and in vitro clastogenicity mouse lymphoma assay, tested in the absence and presence of a metabolic activation system. Etravirine did not induce chromosomal damage in the in vivo micronucleus test in mice.

Impairment of Fertility

No effects on fertility and early embryonic development were observed when etravirine was tested in rats at maternal doses up to 500 mg per kg per day, resulting in systemic drug exposure up to the recommended human dose (400 mg per day).

14 CLINICAL STUDIES

14.1 Treatment-Experienced Adult Subjects

The clinical efficacy of INTELENCE® is derived from the analyses of 48-week data from 2 ongoing, randomized, double-blinded, placebo-controlled, Phase 3 trials, TMC125-C206 and TMC125-C216 (DUET-1 and DUET-2). These trials are identical in design and the results below are pooled data from the two trials.

TMC125-C206 and TMC125-C216 are Phase 3 studies designed to evaluate the safety and antiretroviral activity of INTELENCE® in combination with a background regimen (BR) as compared to placebo in combination with a BR. Eligible subjects were treatment-experienced HIV-1-infected patients with plasma HIV-1 RNA greater than 5000 copies per mL while on an antiretroviral regimen for at least 8 weeks. In addition, subjects had 1 or more NNRTI resistance-associated mutations at screening or from prior genotypic analysis, and 3 or more of the following primary PI mutations at screening: D30N, V32I, L33F, M46I/L, I47A/V, G48V, I50L/V, V82A/F/L/S/T, I84V, N88S, or L90M. Randomization was stratified by the intended use of enfuvirtide (ENF) in the BR, previous use of darunavir/ritonavir (DRV/rtv), and screening viral load. Virologic response was defined as HIV-1 RNA less than 50 copies per mL at Week 48.

All study subjects received DRV/rtv as part of their BR, and at least 2 other investigator-selected antiretroviral drugs (N[t]RTIs with or without ENF). Of INTELENCE®-treated subjects, 25.5% used ENF for the first time (de novo) and 20.0% re-used ENF. Of placebo-treated subjects, 26.5% used de novo ENF and 20.4% re-used ENF.

In the pooled analysis for TMC125-C206 and TMC125-C216, demographics and baseline characteristics were balanced between the INTELENCE® arm and the placebo arm. Table 10 displays selected demographic and baseline disease characteristics of the subjects in the INTELENCE® and placebo arms.

Table 10: Demographic and Baseline Disease Characteristics of Subjects in the TMC125-C206 and TMC125-C216 Trials (Pooled Analysis)
 | Pooled TMC125-C206 and TMC125-C216 Trials
 | INTELENCE® + BR N=599 | Placebo + BR N=604
Demographic Characteristics
Median Age, years (range) | 46 (18–77) | 45 (18–72)
Sex
Male | 90.0% | 88.6%
Female | 10.0% | 11.4%
Race
White | 70.1% | 69.8%
Black | 13.2% | 13.0%
Hispanic | 11.3% | 12.2%
Asian | 1.3% | 0.6%
Other | 4.1% | 4.5%
Baseline Disease Characteristics
Median Baseline Plasma HIV-1 RNA (range), log10 copies/mL | 4.8 (2.7–6.8) | 4.8 (2.2–6.5)
Percentage of Subjects with Baseline Viral Load:
< 30,000 copies/mL | 27.5% | 28.8%
≥ 30,000 copies/mL and
< 100,000 copies/mL | 34.4% | 35.3%
≥ 100,000 copies/mL | 38.1% | 35.9%
Median Baseline CD4+ Cell Count (range), cells/mm^3 | 99 (1–789) | 109 (0–912)
Percentage of Subjects with Baseline CD4+ Cell Count:
< 50 cells/mm^3 | 35.6% | 34.7%
≥ 50 cells/mm^3 and < 200 cells/mm^3 | 34.8% | 34.5%
≥ 200 cells/mm^3 | 29.6% | 30.8%
Median (range) Number of Primary PI Mutations [IAS-USA primary PI mutations [August/September 2007]: D30N, V32I, L33F, M46I/L, I47A/V, G48V, I50L/V, I54L/M, L76V, V82A/F/L/S/T, I84V, N88S, L90M] | 4 (0–7) | 4 (0–8)
Percentage of Subjects with Previous Use of NNRTIs:
0 | 8.2% | 7.9%
1 | 46.9% | 46.7%
>1 | 44.9% | 45.4%
Percentage of Subjects with Previous Use of the following NNRTIs:
Efavirenz | 70.3% | 72.5%
Nevirapine | 57.1% | 58.6%
Delavirdine | 13.7% | 12.6%
Median (range) Number of NNRTI RAMs [Tibotec NNRTI RAMs [June 2008]: A98G, V90I, L100I, K101E/H/P/Q, K103H/N/S/T, V106A/M/I, V108I, E138A/G/K/Q, V179D/E/F/G/I/T, Y181C/I/V, Y188C/H/L, V189I, G190A/C/E/Q/S, H221Y, P255H, F227C/L, M230I/L, P236L, K238N/T, Y318F] | 2 (0–8) | 2 (0–7)
Median Fold Change of the Virus for the Following NNRTIs:
Delavirdine | 27.3 | 26.1
Efavirenz | 63.9 | 45.4
Etravirine | 1.6 | 1.5
Nevirapine | 74.3 | 74.0
Percentage of Subjects with Previous Use of a Fusion Inhibitor | 39.6% | 42.2%
Percentage of Subjects with a Phenotypic Sensitivity Score (PSS) for the background therapy [The PSS was calculated for the background therapy (as determined on Day 7). Percentages are based on the number of subjects with available phenotype data. For fusion inhibitors (enfuvirtide), subjects were considered resistant if the drug was used in previous therapy up to baseline. INTELENCE® is not included in this calculation.] of:
0 | 17.0% | 16.2%
1 | 36.5% | 38.7%
2 | 26.9% | 27.8%
≥ 3 | 19.7% | 17.3%
RAMs = Resistance-Associated Mutations, BR=background regimen
FC = fold change in EC50

Efficacy at Week 48 for subjects in the INTELENCE® and placebo arms for the pooled TMC125-C206 and TMC125-C216 study populations are shown in Table 11.

Table 11: Outcomes of Treatment at Week 48 of the TMC125-C206 and TMC125-C216 Trials (Pooled Analysis)
 | Pooled TMC125-C206 and TMC125-C216 Trials
 | INTELENCE® + BR N=599 | Placebo + BR N=604
Virologic Responders at Week 48 Viral Load < 50 HIV-1 RNA copies/mL | 359 (60%) | 232 (38%)
Virologic Failures (VF) at Week 48 Viral Load ≥ 50 HIV-1 RNA copies/mL | 123 (21%) | 201 (33%)
Death | 11 (2%) | 19 (3%)
Discontinuations before Week 48:
due to VF | 58 (10%) | 110 (18%)
due to Adverse Events | 31 (5%) | 14 (2%)
due to other reasons | 17 (3%) | 28 (5%)
BR=background regimen

At Week 48, 70.8% of INTELENCE®-treated subjects achieved HIV-1 RNA less than 400 copies per mL as compared to 46.4% of placebo-treated subjects. The mean decrease in plasma HIV-1 RNA from baseline to Week 48 was -2.23 log10 copies per mL for INTELENCE®-treated subjects and -1.46 log10 copies per mL for placebo-treated subjects. The mean CD4+ cell count increase from baseline for INTELENCE®-treated subjects was 96 cells per mm^3 and 68 cells per mm^3 for placebo-treated subjects.

Of the study population who either re-used or did not use ENF, 57.4% of INTELENCE®-treated subjects and 31.7% of placebo-treated subjects achieved HIV-1 RNA less than 50 copies per mL. Of the study population using ENF de novo, 67.3% of INTELENCE®-treated subjects and 57.2% of placebo-treated subjects achieved HIV-1 RNA less than 50 copies per mL.

Treatment-emergent CDC category C events occurred in 4% of INTELENCE®-treated subjects and 8.4% of placebo-treated subjects.

Study TMC125-C227 was a randomized, exploratory, active-controlled, open-label, Phase 2b trial. Eligible subjects were treatment-experienced, PI-naïve HIV-1-infected patients with genotypic evidence of NNRTI resistance at screening or from prior genotypic analysis. The virologic response was evaluated in 116 subjects who were randomized to INTELENCE® (59 subjects) or an investigator-selected PI (57 subjects), each given with 2 investigator-selected N(t)RTIs. INTELENCE®-treated subjects had lower antiviral responses associated with reduced susceptibility to the N(t)RTIs and to INTELENCE® as compared to the control PI-treated subjects.

14.2 Treatment-Experienced Pediatric Subjects (6 years to less than 18 years of age)

TMC125-C213, a single-arm, Phase 2 trial evaluating the pharmacokinetics, safety, tolerability, and efficacy of INTELENCE® enrolled 101 antiretroviral treatment-experienced HIV-1 infected pediatric subjects 6 years to less than 18 years of age and weighing at least 16 kg. Subjects eligible for this trial were on an antiretroviral regimen with confirmed plasma HIV-1 RNA of at least 500 copies per mL and viral susceptibility to INTELENCE® at screening.

The median baseline plasma HIV-1 RNA was 3.9 log10 copies per mL, and the median baseline CD4 cell count was 385 × 10^6 cells per mm^3.

At Week 24, 52% of all pediatric subjects had HIV-1 RNA less than 50 copies per mL. The proportion of pediatric subjects with HIV-1 RNA less than 400 copies per mL was 67%. The mean CD4 cell count increase from baseline was 112 × 10^6 cells per mm^3.

16 HOW SUPPLIED/STORAGE AND HANDLING

INTELENCE® 100 mg tablets are supplied as white to off-white, oval tablets containing 100 mg of etravirine. Each tablet is debossed with "TMC125" on one side and "100" on the other side.

Bottles of 120 | NDC 54868-5864-0

INTELENCE® 200 mg tablets are supplied as white to off-white, biconvex, oblong tablets containing 200 mg of etravirine. Each tablet is debossed with "T200" on one side.

Bottles of 60 | NDC 54868-6368-0

STORAGE AND HANDLING

Store INTELENCE® tablets at 25°C (77°F); with excursions permitted to 15°to 30°C (59°to 86°F) [see USP controlled room temperature]. Store in the original bottle. Keep the bottle tightly closed in order to protect from moisture. Do not remove the desiccant pouches.

17 PATIENT COUNSELING INFORMATION

See FDA-approved patient labeling (Patient Information).

A statement to patients and healthcare providers is included on the product's bottle label: ALERT: Find out about medicines that should NOT be taken with INTELENCE® from your healthcare provider. A Patient Package Insert for INTELENCE® is available for patient information.

Patients should be informed that INTELENCE® is not a cure for HIV infection and that they may continue to develop opportunistic infections and other complications associated with HIV disease. Patients should be told that sustained decreases in plasma HIV RNA have been associated with a reduced risk of progression to AIDS and death. Patients should remain under the care of a physician while using INTELENCE®.

Patients should be advised to avoid doing things that can spread HIV-1 infection to others. Patients should be advised to practice safe sex and to use latex or polyurethane condoms to lower the chance of sexual contact with any body fluids such as semen, vaginal secretions or blood. Patients should also be advised to never re-use or share needles or other injection equipment, or share personal items that can have blood or body fluids on them, such as toothbrushes and razor blades.

Patients should be advised to take INTELENCE® following a meal twice a day as prescribed. The type of food does not affect the exposure to etravirine.

Patients should be instructed to swallow the INTELENCE® tablet(s) whole with a liquid such as water. Patients should be instructed not to chew the tablets. Patients who are unable to swallow the INTELENCE® tablet(s) whole may disperse the tablet(s) in a glass of water. The patient should be instructed to do the following:

- place the tablet(s) in 5 mL (1 teaspoon) of water, or at least enough liquid to cover the medication,
- stir well until the water looks milky,
- if desired, add more water or alternatively orange juice or milk (patients should not place the tablets in orange juice or milk without first adding water). The use of grapefruit juice or warm (greater than 104°F; greater than 40°C) or carbonated beverages should be avoided.
- drink it immediately,
- rinse the glass several times with water, orange juice, or milk and completely swallow the rinse each time to make sure the patient takes the entire dose.

INTELENCE® must always be used in combination with other antiretroviral drugs. Patients should not alter the dose of INTELENCE® or discontinue therapy with INTELENCE® without consulting their physician.

If the patient misses a dose of INTELENCE® within 6 hours of the time it is usually taken, the patient should take INTELENCE® following a meal as soon as possible, and then take the next dose of INTELENCE® at the regularly scheduled time. If a patient misses a dose of INTELENCE® by more than 6 hours of the time it is usually taken, the patient should not take the missed dose and simply resume the usual dosing schedule. Inform the patient that he or she should not take more or less than the prescribed dose of INTELENCE® at any one time.

INTELENCE® may interact with many drugs; therefore, patients should be advised to report to their healthcare provider the use of any other prescription or nonprescription medication or herbal products, including St. John's wort.

Patients should be informed that severe and potentially life-threatening rash has been reported with INTELENCE®. Rash has been reported most commonly in the first 6 weeks of therapy. Patients should be advised to immediately contact their healthcare provider if they develop rash. Instruct patients to immediately stop taking INTELENCE® and seek medical attention if they develop a rash associated with any of the following symptoms as it may be a sign of a more serious reaction such as Stevens-Johnson syndrome, toxic epidermal necrolysis or severe hypersensitivity: fever, generally ill feeling, extreme tiredness, muscle or joint aches, blisters, oral lesions, eye inflammation, facial swelling, swelling of the eyes, lips, mouth, breathing difficulty, and/or signs and symptoms of liver problems (e.g., yellowing of your skin or whites of your eyes, dark or tea colored urine, pale colored stools/bowel movements, nausea, vomiting, loss of appetite, or pain, aching or sensitivity on your right side below your ribs). Patients should understand that if severe rash occurs, they will be closely monitored, laboratory tests will be ordered and appropriate therapy will be initiated.

Patients should be informed that redistribution or accumulation of body fat may occur in patients receiving antiretroviral therapy, including INTELENCE®, and that the cause and long-term health effects of these conditions are not known at this time.

Product of Belgium
Finished Product Manufactured by:
Janssen Cilag S.p.A., Latina, Italy
Manufactured for:
Janssen Therapeutics, Division of Janssen Products, LP, Titusville NJ 08560

© Janssen Pharmaceuticals, Inc. 2008

Distributed by:
Physicians Total Care, Inc.
Tulsa, Oklahoma 74146

Patient Information
INTELENCE® (in-tel-ence)
(etravirine) tablets

Important: Ask your doctor or pharmacist about medicines that should not be taken with INTELENCE®. For more information, see the section "What should I tell my doctor before taking INTELENCE®?".

Read this Patient Information before you start taking INTELENCE® and each time you get a refill. There may be new information. This information does not take the place of talking with your doctor about your medical condition or your treatment. You and your doctor should discuss your treatment with INTELENCE® when you start taking it and at regular checkups. You should not change or stop treatment without first talking with your doctor.

What is INTELENCE®?

- INTELENCE® is a prescription HIV medicine that:
  - is used with other HIV medicines to treat HIV (Human Immunodeficiency Virus) infection in adults and children 6 years of age and older. HIV is the virus that causes AIDS (Acquired Immune Deficiency Syndrome). INTELENCE® is a type of HIV medicine called a non-nucleoside reverse transcriptase inhibitor (NNRTI).
  - is used in people who are already taking or have taken NNRTI and other HIV medicines and these medicines are not controlling their HIV infection.
- It is not known if INTELENCE® is safe and effective in children less than 6 years of age.

When used with other HIV medicines, INTELENCE® may:

1. Reduce the amount of HIV in your blood (called "viral load").
2. Help increase the number of CD4 (T) cells in your blood which help fight off other infections.
  Reducing the amount of HIV and increasing the CD4 (T) cell count may improve your immune system. This may reduce your risk of death or infections that can happen when your immune system is weak (opportunistic infections).

INTELENCE® does not cure HIV infection or AIDS.

You must stay on continuous HIV therapy to control HIV infection and decrease HIV-related illnesses.

Avoid doing things that can spread HIV-1 infection to others:

- Do not share or re-use needles or other injection equipment.
- Do not share personal items that can have blood or body fluids on them, like toothbrushes and razor blades.
- Do not have any kind of sex without protection. Always practice safe sex by using a latex or polyurethane condom to lower the chance of sexual contact with semen, vaginal secretions, or blood.

Ask your doctor if you have any questions on how to prevent passing HIV to other people.

What should I tell my doctor before taking INTELENCE®?

Before taking INTELENCE® tell your doctor if you:

- have had or currently have liver problems, including hepatitis B or C.
- have any other medical conditions.
- are pregnant or plan to become pregnant. It is not known if INTELENCE® will harm your unborn baby.
  Pregnancy Registry: There is a pregnancy registry for women who take antiviral medicines during pregnancy. The purpose of this registry is to collect information about the health of you and your baby. Talk to your doctor about how you can take part in this registry.
- are breastfeeding or plan to breastfeed. Do not breastfeed if you take INTELENCE®. You should not breastfeed if you have HIV because of the risk of passing HIV to your baby. Talk with your doctor about the best way to feed your baby.

Tell your doctor about all the medicines you take, including prescription and nonprescription medicines, vitamins, and herbal supplements, including St. John's wort (Hypericum perforatum). Some medicines may interact with INTELENCE®.

INTELENCE® may affect the way other medicines work, and other medicines may affect how INTELENCE® works. Taking INTELENCE® and certain other medicines may cause serious side effects. If you take certain medicines with INTELENCE®, then the amount of INTELENCE® in your body may be too low and INTELENCE® may not work to help reduce your HIV viral load. The HIV virus in your body may become resistant to INTELENCE® or other HIV medicines that are like it.

Tell your doctor if you take other HIV medicines. Some HIV medicines should not be taken with INTELENCE®.

Tell your doctor if you take:

- an antiarrhythmic to treat abnormal heart rhythms-amiodarone (Cordarone®, Pacerone®), bepridil (Vascor®), digoxin (Lanoxin®), disopyramide (Norpace®), flecainide (Tambocor™), lidocaine (LidoPen®, Xylocaine®), mexiletine (Mexitil®), propafenone (Rythmol SR®), quinidine (Duraquin®, Quinaglute®)
- an anticoagulant to prevent blood clots-warfarin (Coumadin®)
- an anti-seizure medicine to treat epilepsy or prevent seizures-carbamazepine (Tegretol®, Tegretol-XR®, Carbatrol®, Equetro®, Teril®, Epitol®), phenobarbital (Luminal®, Solfoton®), phenytoin (Dilantin®, Dilantin-125®, Phenytek®)
- an antifungal to treat a fungal infection-fluconazole (Diflucan®), itraconazole (Onmel®, Sporanox®), ketoconazole (Nizoral®), posaconazole (Noxafil®), voriconazole (Vfend®)
- an anti-infective to treat a bacterial infection-clarithromycin (Biaxin®, Biaxin XL®)
- an antimycobacterial to treat a bacterial infection, including tuberculosis (TB)-rifabutin (Mycobutin®), rifampin (Rifadin®, Rifater®, Rifamate®, Rimactane®), rifapentine (Priftin®)
- a benzodiazepine to treat trouble with sleeping and/or anxiety-diazepam (Diastat®, Valium®)
- a corticosteroid to treat inflammation or asthma-dexamethasone (Decadron®)
- an HMG-CoA reductase inhibitor to lower cholesterol levels-atorvastatin (Caduet®, Lipitor®), fluvastatin (Lescol®), lovastatin (Advicor®, Altoprev®, Mevacor®), pitavastatin (Livalo®), rosuvastatin (Crestor®), simvastatin (Juvisync®, Simcor®, Vytorin®, Zocor®)
- an immunosuppressant to prevent organ transplant rejection-cyclosporine (Gengraf®, Sandimmune®, Neoral®), sirolimus (Rapamune®), tacrolimus (Prograf®)
- a medicine to treat narcotic withdrawal and dependence-buprenorphine (Buprenex®, Butrans®, Subutex®), buprenorphine/naloxone (Suboxone®), methadone (Dolophine®, Methadose®)
- a PDE-5 inhibitor to treat erectile dysfunction and/or pulmonary arterial hypertension-sildenafil (Revatio®, Viagra®), tadalafil (Adcirca®, Cialis®), vardenafil (Levitra®, Staxyn™)
- a platelet aggregation inhibitor to prevent blood clots-clopidogrel (Plavix®)

Ask your doctor or pharmacist if you are not sure if your medicine is one that is listed above.

Know the medicines you take. Keep a list of your medicines and show it to your doctor and pharmacist when you get a new medicine.

Your doctor and your pharmacist can tell you if you can take these medicines with INTELENCE®. Do not start any new medicines while you are taking INTELENCE® without first talking with your doctor or pharmacist. You can ask your doctor or pharmacist for a list of medicines that can interact with INTELENCE®.

How should I take INTELENCE®?

- Stay under the care of your doctor during treatment with INTELENCE®.
- Take INTELENCE® tablets every day exactly as prescribed by your doctor.
- Your doctor will tell you how many INTELENCE® tablets to take and when to take them. Talk to your doctor if you have questions about when to take INTELENCE®.
- INTELENCE® is taken two times each day.
  - If your child takes INTELENCE®, your doctor will prescribe the right dose based on your child's weight.
- Always take INTELENCE® following a meal. Do not take INTELENCE® on an empty stomach. INTELENCE® may not work as well if you take it on an empty stomach.
- Do not change your dose or stop taking INTELENCE® without first talking with your doctor. See your doctor regularly while taking INTELENCE®.
- Swallow INTELENCE® whole, with a glass of water. Do not chew the tablet(s).
- If you are unable to swallow INTELENCE® tablets whole, you may take your dose of INTELENCE® as follows:
  Step 1: Measure approximately 5 mL (1 teaspoon) of water and pour into a cup.
  Step 2: Place the tablets in the cup containing 5 mL of water. If needed, add more water to cover the tablets. Do not put the tablets in other liquids.
  Step 3: Stir well until the water looks milky.
  Step 4: At this step, you may add a small amount of water, orange juice or milk to make it easier to take.
  Step 5: Drink right away.
  Step 6: Add more water, orange juice or milk to the cup to rinse the cup several times and completely swallow each time to make sure you take your entire dose of INTELENCE®.
- Avoid using grapefruit juice or warm (more than 104°F or 40°C) or carbonated beverages when taking INTELENCE® tablets.
- When your supply of INTELENCE® starts to run low, get more from your doctor or pharmacy. It is important not to run out of INTELENCE®. The amount of HIV in your blood may increase if the medicine is stopped even for a short time.
- If you miss a dose of INTELENCE® within 6 hours of the time you usually take it, take your dose of INTELENCE® following a meal as soon as possible. Then, take your next dose of INTELENCE® at the regularly scheduled time. If you miss a dose of INTELENCE® by more than 6 hours of the time you usually take it, wait and then take the next dose of INTELENCE® at the regularly scheduled time.
- Do not take more than your prescribed dose to make up for a missed dose.
- If you take too much INTELENCE®, contact your local poison control center or go to the nearest emergency room right away.

What are the possible side effects of INTELENCE®?

INTELENCE® can cause serious side effects including:

- Severe skin rash and allergic reactions. Skin rash is a common side effect of INTELENCE®. Rash can be serious. Call your doctor right away if you get a rash. In some cases, severe rash and allergic reaction may need to be treated in a hospital and may potentially lead to death.
  If you get a rash with any of the following symptoms, stop taking INTELENCE® and call your doctor or get medical help right away:
  - hives or sores in your mouth, or your skin blisters and peels
  - trouble swallowing or breathing
  - swelling of your face, eyes, lips, tongue, or throat
  - fever, yellowing of the skin or whites of the eyes, dark urine, or pain on the right side of the stomach-area (abdominal pain).
- Changes in body fat can happen in people taking HIV medicines. These changes may include an increased amount of fat in the upper back and neck ("buffalo hump"), breast, and around the middle of your body (trunk). Loss of fat from the legs, arms, and face may also happen. The exact cause and long-term health effects of these problems are not known.
- Changes in your immune system (Immune Reconstitution Syndrome) can happen when you start taking HIV medicines. Your immune system may get stronger and begin to fight infections that have been hidden in your body for a long time. Call your doctor right away if you start having any new symptoms after starting your HIV medicine.

In adults, common side effects of INTELENCE® include tingling, numbness, or pain in the hands or feet.

In children, diarrhea is a common side effect of INTELENCE®.

Tell your doctor if you have any side effect that bothers you or that does not go away.

These are not all of the possible side effects with INTELENCE®. For more information, ask your doctor or pharmacist.

Call your doctor for medical advice about side effects. You may report side effects to FDA at 1-800-FDA-1088.

How should I store INTELENCE®?

- Store INTELENCE® tablets at 59°F to 86°F (15°C to 30°C).
- Keep INTELENCE® in the original bottle given to you by your pharmacist. After opening, keep the bottle tightly closed to protect INTELENCE® from moisture.
- The INTELENCE® bottle contains a desiccant packet to help keep your medicine dry (protect it from moisture). The bottle of 25 mg tablets contains 2 desiccant packets. The bottles of 100 mg and 200 mg tablets contain 3 desiccant packets. Keep the desiccant packets in the bottle. Do not eat the desiccant packets.

Keep INTELENCE® and all medicines out of the reach of children.

General information about INTELENCE®

Medicines are sometimes prescribed for purposes other than those listed in a Patient Information leaflet. Do not use INTELENCE® for a condition for which it was not prescribed. Do not give INTELENCE® to other people even if they have the same condition you have. It may harm them.

This leaflet summarizes the most important information about INTELENCE®. If you would like more information, talk with your doctor. You can ask your doctor or pharmacist for information about INTELENCE® that is written for health professionals. For more information, you may also call Janssen Products, LP at 1-800-526-7736.

What are the ingredients in INTELENCE®?

Active ingredient: etravirine.

25 mg and 100 mg INTELENCE® tablets contain the following inactive ingredients: hypromellose, microcrystalline cellulose, colloidal silicon dioxide, croscarmellose sodium, magnesium stearate and lactose monohydrate

200 mg INTELENCE® tablets contain the following inactive ingredients: hypromellose, silicified microcrystalline cellulose, microcrystalline cellulose, colloidal silicon dioxide, croscarmellose sodium and magnesium stearate.

This Patient Information has been approved by the U.S. Food and Drug Administration.

Product of Belgium
Finished Product Manufactured by:
Janssen Cilag S.p.A., Latina, IT
Manufactured for:
Janssen Therapeutics, Division of Janssen Products, LP, Titusville NJ 08560

INTELENCE® is the registered trademark of Tibotec Pharmaceuticals.

Revised August 2012

© Janssen Pharmaceuticals, Inc. 2008

PRINCIPAL DISPLAY PANEL - 100 mg Bottle Label

120 Tablets
NDC 54868-5864-0

INTELENCE®
(etravirine) tablets

100 mg

Each tablet contains
100 mg of etravirine.

Rx only

PRINCIPAL DISPLAY PANEL - 200 mg Bottle Label

60 Tablets
NDC 54868-6368-0

INTELENCE®
(etravirine) tablets

200 mg

Each tablet contains
200 mg of etravirine.

Rx only